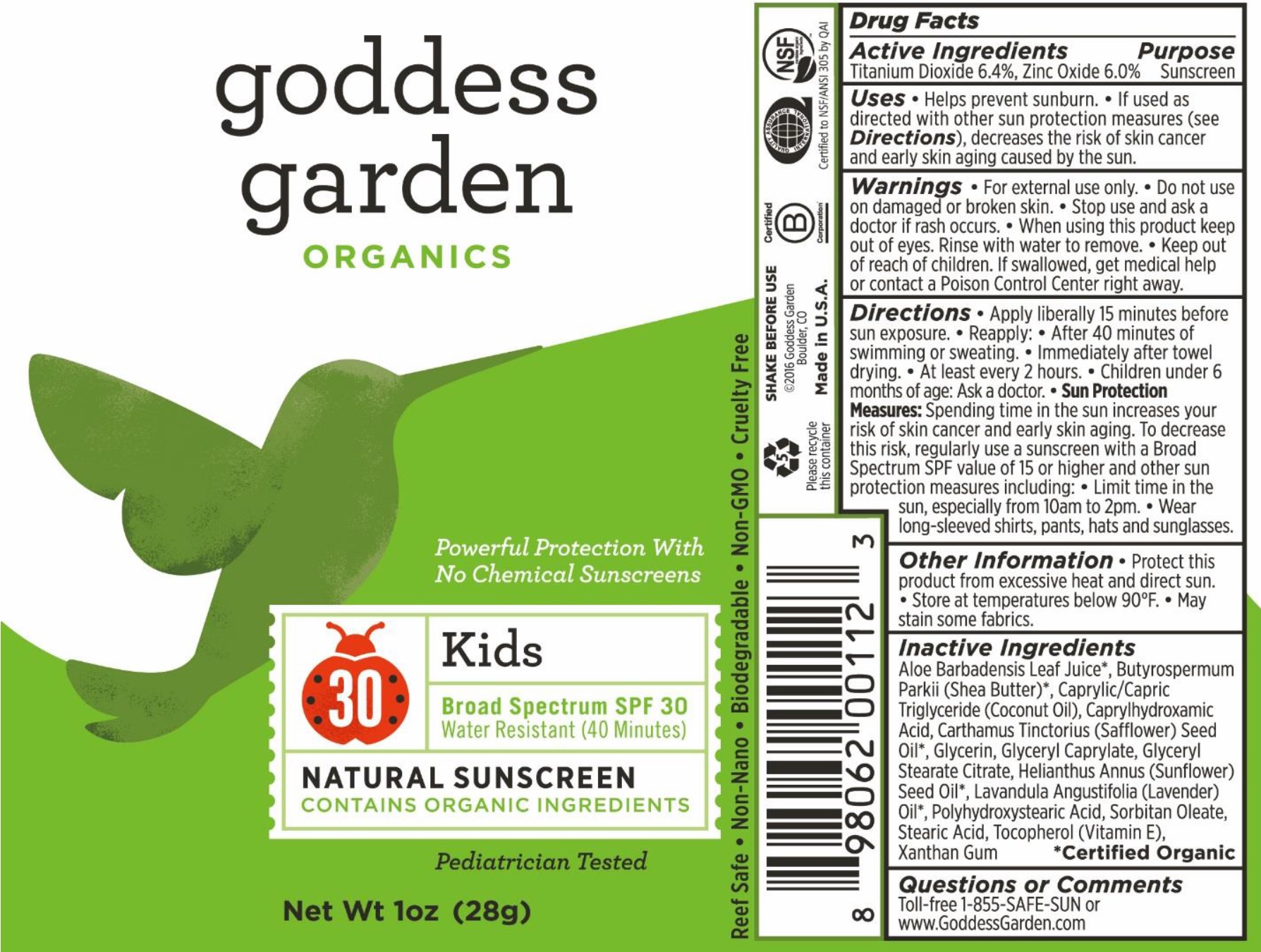 DRUG LABEL: Kids Natural Mineral Sunscreen Broad Spectrum
NDC: 58479-038 | Form: LOTION
Manufacturer: Crossing Cultures LLC dba Goddess Garden
Category: otc | Type: HUMAN OTC DRUG LABEL
Date: 20161201

ACTIVE INGREDIENTS: TITANIUM DIOXIDE 6.4 g/100 g; ZINC OXIDE 6 g/100 g
INACTIVE INGREDIENTS: ALOE VERA LEAF; MEDIUM-CHAIN TRIGLYCERIDES; SHEA BUTTER; CAPRYLHYDROXAMIC ACID; SAFFLOWER OIL; GLYCERIN; GLYCERYL CAPRYLATE; GLYCERYL STEARATE CITRATE; SUNFLOWER OIL; LAVENDER OIL; STEARIC ACID; TOCOPHEROL; XANTHAN GUM; ALUMINUM HYDROXIDE; WATER; LAVANDIN OIL; POLYHYDROXYSTEARIC ACID (2300 MW); SORBITAN MONOOLEATE

Kids Natural Mineral Sunscreen Broad Spectrum SPF 30 Lotion

Active Ingredients

Titanium Doxide 6.4%, Zinc Oxide 6.0%

Purpose

Sunscreen

Uses

- Helps prevent sunburn.
- If used as directed with other sun protection measures (see Directions), decreases the risk of skin cancer and early skin aging caused by the sun.

Warnings

- For external use only.

Do not use

on damaged or broken skin.

Stop use and ask a doctor

if rash occurs.

When using this product

keep out of eyes. Rinse with water to remove.

Keep out of reach of children.

If swallowed, get medical help or contact a Poison Control Center right away.

Directions

• Apply liberally 15 minutes before sun exposure. • Reapply: • After 40 minutes of swimming or sweating. • Immediately after towel drying. • At least every 2 hours. • Children under 6 months of age: Ask a doctor. • Sun Protection Measures: Spending time in the sun increases your risk of skin cancer and early skin aging. To decrease this risk, regularly use a sunscreen with a Broad Spectrum SPF value of 15 or higher and other sun protection measures including: • Limit time in the sun, especially from 10am to 2pm. • Wear long-sleeved shirts, pants, hats and sunglasses.

Other Information

• Protect this product from excessive heat and direct sun. • Store at temperatures below 90°F. • May stain some fabrics.

Inactive Ingredients

Aloe Barbadensis Leaf Juice*, Aluminum Hydroxide, Butyrospermum Parkii (Shea Butter)*, Caprylhydroxamic Acid, Caprylic/Capric Triglyceride (Coconut Oil), Carthamus Tinctorius (Safflower) Seed Oil*, Glycerin, Glyceryl Caprylate, Glyceryl Stearate Citrate, Helianthus Annuus (Sunflower) Seed Oil*, Lavandula Angustifolia (Lavender) Oil*, Lavandula Hybrida (Lavandin) Oil*, Polyhydroxystearic Acid, Sorbitan Oleate, Stearic Acid, Tocopherol (Vitamin E), Water, Xanthan Gum *Certified Organic

Questions or Comments

Toll-free 1-855-SAFE-SUN or

www.GoddessGarden.com